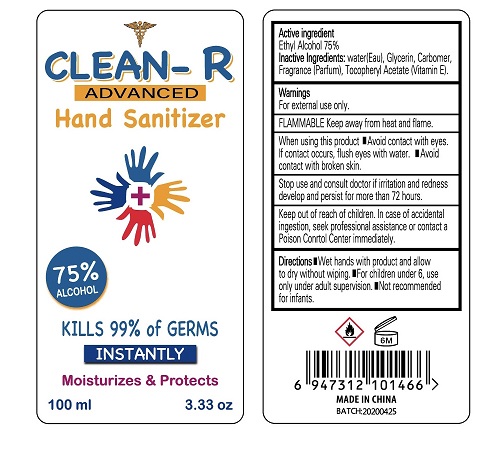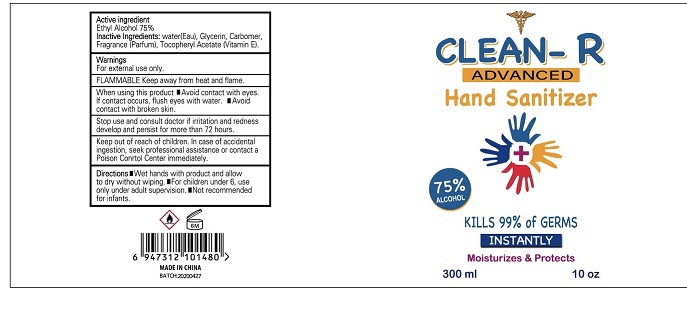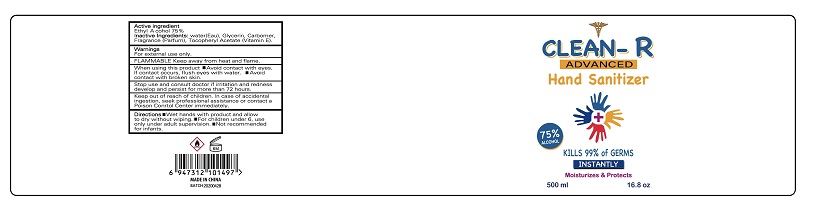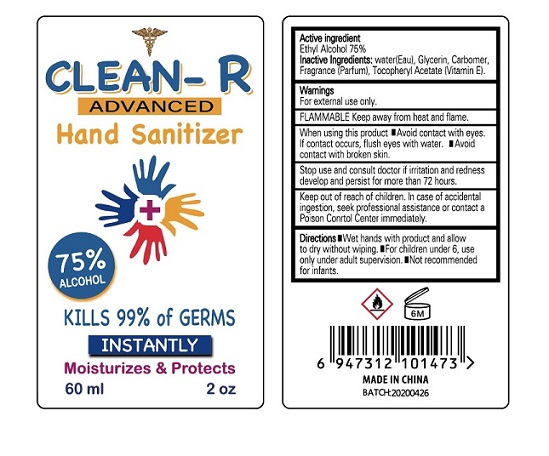 DRUG LABEL: CLEAN-R
NDC: 77594-001 | Form: GEL
Manufacturer: Sure Trade International LLC
Category: otc | Type: HUMAN OTC DRUG LABEL
Date: 20200508

ACTIVE INGREDIENTS: ALCOHOL 75 mL/100 mL
INACTIVE INGREDIENTS: WATER; GLYCERIN; CARBOMER HOMOPOLYMER, UNSPECIFIED TYPE; .ALPHA.-TOCOPHEROL ACETATE

Active Ingredient

Ethyl Alcohol 75%

Warnings

For external use only.

FLAMMABLE. Keep away from heat or flame.

When using this product

- Avoid contact with eyes. If contact occurs, flush eyes with water.
- Avoid contact with broken skin.

Stop use and consult doctor if irritation and redness develop and persist for more than 72 hours.

Keep out of reach of children. In case of accidental ingestion, seek professional assistance or contact a Poison Control Center immediately.

Directions

- Wet hands with product and allow to dry without wiping.
- For children under 6, use only under adult supervision.
- Not recommended for infants.

Inactive ingredients

Water (Eau), Glycerin, Carbomer, Fragrance (Parfum), Tocopheryl Acetate (Vitamin E).

Package Label - Principal Display Panel

Label 60 mL

Label 100 mL

Label 300 mL

Label 500 mL